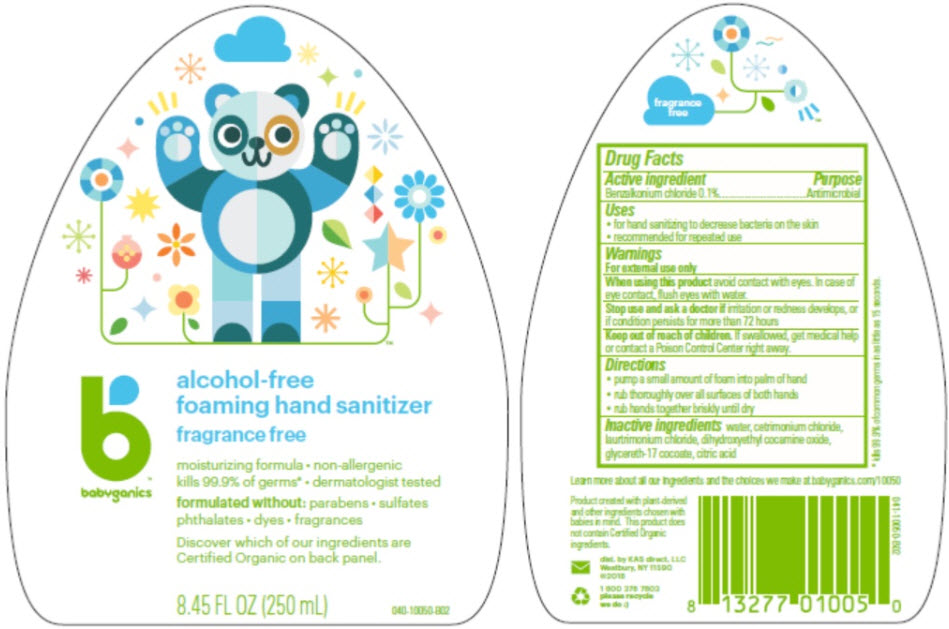 DRUG LABEL: BabyGanics Alcohol Free Foaming Hand Sanitizer
NDC: 59062-3000 | Form: LIQUID
Manufacturer: KAS Direct LLC dba BabyGanics
Category: otc | Type: HUMAN OTC DRUG LABEL
Date: 20251205

ACTIVE INGREDIENTS: BENZALKONIUM CHLORIDE 0.1 mg/1 mL
INACTIVE INGREDIENTS: WATER; CETRIMONIUM CHLORIDE; LAURTRIMONIUM CHLORIDE; DIHYDROXYETHYL COCAMINE OXIDE; GLYCERETH-17 COCOATE

BabyGanics™ Alcohol Free Foaming Hand Sanitizer

Drug Facts

Active ingredient

Benzalkonium chloride 0.1%

Purpose

Antimicrobial

Uses

- for hand sanitizing to decrease bacteria on the skin
- recommended for repeated use

Warnings

For external use only

When using this product avoid contact with eyes. In case of eye contact, flush eyes with water.

Stop use and ask a doctor if irritation or redness develops, or if condition persists for more than 72 hours

Keep out of reach of children. If swallowed, get medical help or contact a Poison Control Center right away.

Directions

- pump a small amount of foam into palm of hand
- rub thoroughly over all surfaces of both hands
- rub hands together briskly until dry

Inactive ingredients

water, cetrimonium chloride, laurtrimonium chloride, dihydroxyethyl cocamine oxide, glycereth-17 cocoate, citric acid

dist. by KAS direct, LLC
Westbury, NY 11590

PRINCIPAL DISPLAY PANEL - 250 mL Bottle Label

babyganics™
alcohol-free
foaming hand sanitizer
fragrance free

moisturizing formula • non-allergenic
kills 99.9% of germs* • dermatologist tested

formulated without: parabens • sulfates
phthalates • dyes • fragrances

Discover which of our ingredients are
Certified Organic on back panel.

8.45 FL OZ (250 mL)
040-10050-B02